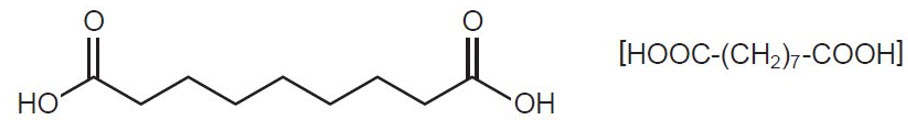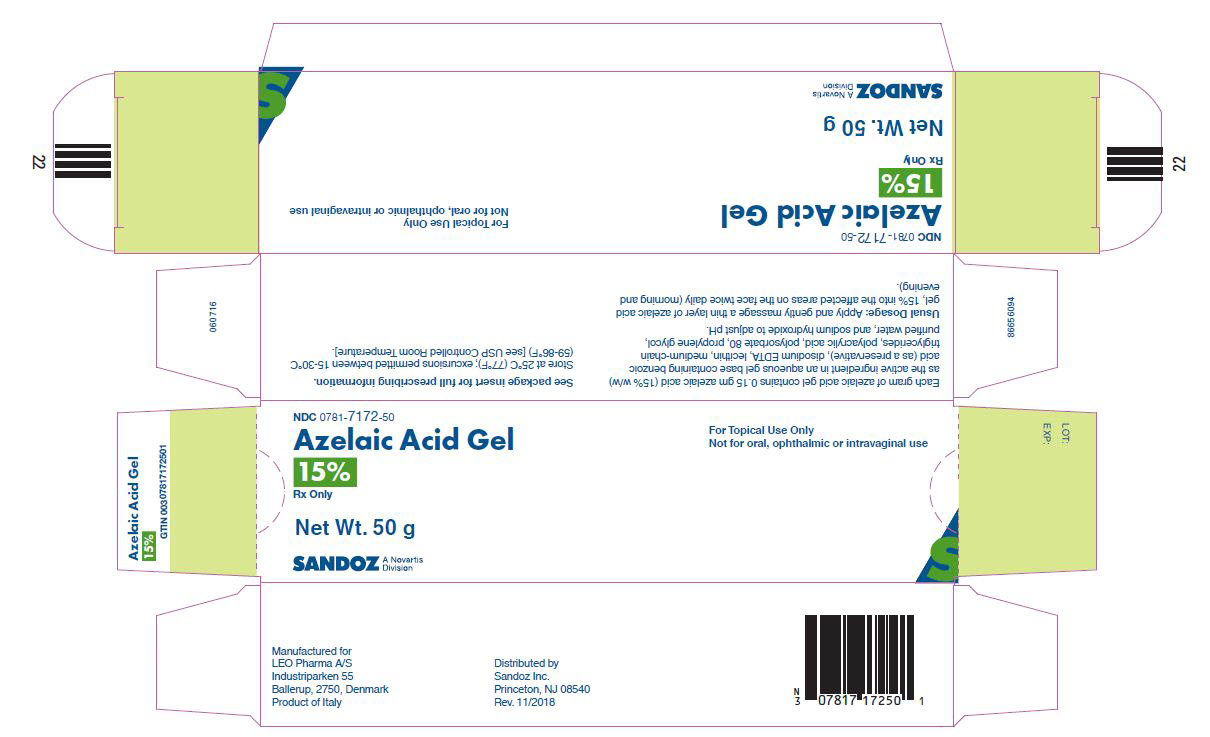 DRUG LABEL: Azelaic Acid Gel
NDC: 0781-7172 | Form: GEL
Manufacturer: Sandoz Inc.
Category: prescription | Type: HUMAN PRESCRIPTION DRUG LABEL
Date: 20211111

ACTIVE INGREDIENTS: AZELAIC ACID 0.15 g/1 g
INACTIVE INGREDIENTS: BENZOIC ACID; EDETATE DISODIUM; 1,2-DIARACHIDOYL-SN-GLYCERO-3-PHOSPHOCHOLINE; MEDIUM-CHAIN TRIGLYCERIDES; POLYACRYLIC ACID (250000 MW); POLYSORBATE 80; PROPYLENE GLYCOL; SODIUM HYDROXIDE; WATER

HIGHLIGHTS OF PRESCRIBING INFORMATION

These highlights do not include all the information needed to use AZELAIC ACID GEL safely and effectively. See full prescribing information for AZELAIC ACID GEL.
AZELAIC ACID gel, for topical use
Initial U.S. Approval: 1995

1 INDICATIONS AND USAGE

Azelaic acid gel, 15% is indicated for topical treatment of the inflammatory papules and pustules of mild to moderate rosacea (1).

Limitations of Use

Efficacy for treatment of erythema in rosacea in the absence of papules and pustules has not been evaluated. (1)

2 DOSAGE AND ADMINISTRATION

- Apply a thin layer twice daily to affected area(s). (2)
- Use only very mild soaps or soapless cleansing lotion and pat dry with a soft towel before applying azelaic acid gel. (2)
- Wash hands immediately following application. (2)
- Cosmetics may be applied after the application of azelaic acid gel has dried. (2)
- Avoid use of alcoholic cleansers, tinctures and astringents, abrasives and peeling agents. (2)
- For topical use. (2)
- Not for oral, ophthalmic or intravaginal use. (2)

3 DOSAGE FORMS AND STRENGTHS

Gel, 15% (3)

4 CONTRAINDICATIONS

None. (4)

5 WARNINGS AND PRECAUTIONS

- Hypersensitivity: Hypersensitivity reactions, including cases of angioedema, eye swelling, facial swelling, dyspnea, urticaria, and adverse skin reactions, have been reported. In case of known hypersensitivity to any component of the gel, avoid the use of azelaic acid gel. If hypersensitivity develops, discontinue treatment and institute appropriate therapy. (5.1)
- Skin Reactions: Skin irritation (i.e. pruritus, burning or stinging) may occur, usually during the first few weeks of treatment. If sensitivity or severe irritation develops and persists, discontinue treatment and institute appropriate therapy. (5.2)
- Hypopigmentation: Isolated cases of hypopigmentation occurred after azelaic acid use. Monitor patients with dark complexion for early signs of hypopigmentation (5.2)
- Eye and Mucous Membrane Irritation: azelaic acid gel has been reported to cause irritation of the eyes. Avoid contact with the eyes and mucous membranes. (5.3)
- Exacerbation of Asthma: Consult a physician if asthma is exacerbated with azelaic acid gel use. (5.4)

6 ADVERSE REACTIONS

The most common adverse reactions are burning/stinging/tingling (29%), pruritus (11%), scaling/dry skin/xerosis (8%) and erythema/irritation (4%). (6)

To report SUSPECTED ADVERSE REACTIONS, contact LEO Pharma Inc. at 1-877-494-4536 or FDA at 1-800-FDA-1088 or www.fda.gov/medwatch.

FULL PRESCRIBING INFORMATION

1 INDICATIONS AND USAGE

Azelaic acid gel, 15% is indicated for topical treatment of the inflammatory papules and pustules of mild to moderate rosacea.

Limitations of Use

Although some reduction of erythema which was present in patients with papules and pustules of rosacea occurred in clinical studies, efficacy for treatment of erythema in rosacea in the absence of papules and pustules has not been evaluated.

2 DOSAGE AND ADMINISTRATION

- Cleanse affected area(s) using only very mild soaps or soapless cleansing lotion and pat dry with a soft towel before application of azelaic acid gel.
- Apply and gently massage a thin layer of azelaic acid gel into the affected areas on the face twice daily (morning and evening).
- Wash hands immediately following application of azelaic acid gel.
- Cosmetics may be applied after the application of azelaic acid gel has dried.
- Reassess the diagnosis if no improvement is observed upon completing 12 weeks of therapy.
- Avoid the use of occlusive dressings or wrappings.
- Instruct patients to avoid use of alcoholic cleansers, tinctures and astringents, abrasives and peeling agents.
- For topical use.
- Not for oral, ophthalmic or intravaginal use.

3 DOSAGE FORMS AND STRENGTHS

Azelaic acid gel, 15% is a white to yellowish white opaque gel. Each gram of azelaic acid gel contains 0.15 gm of azelaic acid (15% w/w).

4 CONTRAINDICATIONS

None.

5 WARNINGS AND PRECAUTIONS

5.1 Hypersensitivity

Hypersensitivity reactions, including cases of angioedema, eye swelling, facial swelling, dyspnea, urticaria, and adverse skin reactions, have been reported during post marketing surveillance.

Avoid the use of azelaic acid gel in patients with known hypersensitivity to any component of the gel. If hypersensitivity develops during treatment, discontinue azelaic acid gel and institute appropriate therapy.

5.2 Skin Reactions

Skin irritation (i.e. pruritus, burning or stinging) may occur during use of azelaic acid gel, usually during the first few weeks of treatment. If sensitivity or severe irritation develops and persists, discontinue treatment and institute appropriate therapy.

There have been isolated reports of hypopigmentation after use of azelaic acid. Since azelaic acid has not been well studied in patients with dark complexion, monitor these patients for early signs of hypopigmentation.

5.3 Eye and Mucous Membranes Irritation

Azelaic acid gel has been reported to cause irritation of the eyes. Avoid contact with the eyes, mouth and other mucous membranes. If azelaic acid gel comes in contact with the eyes, wash the eyes with large amounts of water and consult a physician if eye irritation persists [see Adverse Reactions (6.2)].

5.4 Exacerbation of Asthma

Worsening of asthma has been reported in patients using azelaic acid formulations including azelaic acid gel. Consult a physician if asthma is exacerbated with use of azelaic acid gel.

6 ADVERSE REACTIONS

6.1 Clinical Trials Experience

Because clinical trials are conducted under widely varying conditions, adverse reaction rates observed in the clinical trials of a drug cannot be directly compared to rates in the clinical trials of another drug and may not reflect the rates observed in practice.

In two vehicle-controlled and one active-controlled U.S. clinical trials, treatment safety was monitored in 788 subjects who used twice-daily azelaic acid gel for 12 weeks (N=333) or 15 weeks (N=124), or the gel vehicle (N=331) for 12 weeks. In all three trials, the most common treatment-related adverse events were: burning/stinging/tingling (29%), pruritus (11%), scaling/dry skin/xerosis (8%) and erythema/irritation (4%). In the active-controlled trial, overall adverse reactions (including burning, stinging/tingling, dryness/tightness/scaling, itching, and erythema/irritation/redness) were 19.4% (24/124) for azelaic acid gel compared to 7.1% (9/127) for the active comparator gel at 15 weeks.

Table 1: Adverse Events Occurring in ≥1% of Subjects in the Rosacea Trials by Treatment Group and Maximum Intensity [Subjects may have >1 cutaneous adverse event; thus, the sum of the frequencies of preferred terms may exceed the number of subjects with at least 1 cutaneous adverse event.]
 | Azelaic Acid Gel, 15% N=457 (100%) |  |  | Vehicle N=331 (100%)
 | Mild N=99 (22%) | Moderate N=61 (13%) | Severe N=27 (6%) | Mild N=46 (14%) | Moderate N=30 (9%) | Severe N=5 (2%)
Burning/stinging/tingling | 71 (16%) | 42 (9%) | 17 (4%) | 8 (2%) | 6 (2%) | 2 (1%)
Pruritus | 29 (6%) | 18 (4%) | 5 (1%) | 9 (3%) | 6 (2%) | 0 (0%)
Scaling/dry skin/xerosis | 21 (5%) | 10 (2%) | 5 (1%) | 31 (9%) | 14 (4%) | 1 (<1%)
Erythema/irritation | 6 (1%) | 7 (2%) | 2 (<1%) | 8 (2%) | 4 (1%) | 2 (1%)
Contact dermatitis | 2 (<1%) | 3 (1%) | 0 (0%) | 1 (<1%) | 0 (0%) | 0 (0%)
Edema | 3 (1%) | 2 (<1%) | 0 (0%) | 3 (1%) | 0 (0%) | 0 (0%)
Acne | 3 (1%) | 1 (<1%) | 0 (0%) | 1 (<1%) | 0 (0%) | 0 (0%)

In patients using azelaic acid formulations, the following adverse events have been reported: worsening of asthma, vitiligo, depigmentation, small depigmented spots, hypertrichosis, reddening (signs of keratosis pilaris) and exacerbation of recurrent herpes labialis.

Local Tolerability Studies

Azelaic acid gel and its vehicle caused irritant reactions at the application site in human dermal safety studies. Azelaic acid gel caused significantly more irritation than its vehicle in a cumulative irritation study. Some improvement in irritation was demonstrated over the course of the clinical trials, but this improvement might be attributed to subject dropouts. No phototoxicity or photoallergenicity were reported in human dermal safety studies.

6.2 Postmarketing Experience

The following adverse reactions have been identified post approval of azelaic acid gel. Because these reactions are reported voluntarily from a population of uncertain size, it is not always possible to reliably estimate the frequency or establish a causal relationship to drug exposure:

Eyes: iridocyclitis upon accidental exposure of the eyes to azelaic acid gel

Hypersensitivity: angioedema, eye swelling, facial swelling, urticaria.

Respiratory: worsening of asthma, dyspnea, wheezing.

Skin reactions: application site rash.

8 USE IN SPECIFIC POPULATIONS

8.1 Pregnancy

Risk Summary

Azelaic acid is minimally absorbed systemically following topical route of administration, and maternal use is not expected to result in fetal exposure to the drug [see Clinical Pharmacology (12.3)].

In animal reproduction studies, embryofetal toxicity was noted when azelaic acid was administered orally during the period of organogenesis at doses 162, 19, and 65 times the maximum recommended human dose (MRHD) in rats, rabbits, and monkeys, respectively. Maternal toxicity was noted at these doses but no malformations were observed in these embryofetal developmental studies (see Data).

The background risk of major birth defects and miscarriage for the indicated population is unknown. All pregnancies have a background risk of birth defect, loss, or other adverse outcomes. In the U.S. general population, the estimated background risk of major birth defects and miscarriage in clinically recognized pregnancies is 2 to 4% and 15 to 20%, respectively.

Data

Animal Data

Dermal embryofetal developmental toxicology studies have not been performed with azelaic acid, 15% gel. Oral embryofetal developmental studies were conducted with azelaic acid in rats, rabbits, and cynomolgus monkeys. Azelaic acid was administered during the period of organogenesis in all three animal species. Embryotoxicity was observed in rats, rabbits, and monkeys at oral doses of azelaic acid that generated some maternal toxicity. Embryotoxicity was observed in rats given 2500 mg/kg/day [162 times the MRHD based on body surface area (BSA) comparison], rabbits given 150 or 500 mg/kg/day (19 or 65 times the MRHD based on BSA comparison) and cynomolgus monkeys given 500 mg/kg/day (65 times the MRHD based on BSA comparison) azelaic acid. No malformations were observed in the oral embryofetal developmental studies conducted in rats, rabbits and cynomolgus monkeys.

An oral peri- and post-natal developmental study was conducted in rats. Azelaic acid was administered from gestational day 15 through day 21 postpartum up to a dose level of 2500 mg/kg/day. Embryotoxicity was observed in rats at an oral dose of 2500 mg/kg/day (162 times the MRHD based on BSA comparison) that generated some maternal toxicity. In addition, slight disturbances in the post-natal development of fetuses was noted in rats at oral doses that generated some maternal toxicity (500 and 2500 mg/kg/day; 32 and 162 times the MRHD based on BSA comparison). No effects on sexual maturation of the fetuses were noted in this study.

8.2 Lactation

Risk Summary

Azelaic acid is naturally present in human milk. When used as prescribed, azelaic acid is unlikely to be absorbed through the skin in clinically relevant amounts to cause a change in azelaic acid concentration in milk or milk production; therefore, breastfeeding is not expected to result in exposure of the infant to azelaic acid gel. The developmental and health benefits of breastfeeding should be considered along with the mother's clinical need for azelaic acid gel and any potential adverse effects on the breastfed child from azelaic acid gel or from the underlying maternal condition.

8.4 Pediatric Use

The safety and effectiveness of azelaic acid gel have not been established in pediatric patients.

8.5 Geriatric Use

Clinical studies of azelaic acid gel did not include sufficient numbers of subjects aged 65 and over to determine if they respond differently than younger subjects.

11 DESCRIPTION

Azelaic acid gel, 15%, is an aqueous gel which contains azelaic acid, a naturally-occurring saturated dicarboxylic acid. It is for topical use. Chemically, azelaic acid is 1,7-heptanedicarboxylic acid. The molecular formula for azelaic acid is C9 H16 O4. It has the following structure:

Azelaic acid has a molecular weight of 188.22. It is a white, odorless crystalline solid. It is poorly soluble in water at 20°C (0.24%) but freely soluble in boiling water and in ethanol.

Azelaic acid gel, 15% is a white to yellowish white opaque gel for topical use; each gram contains 0.15 gm azelaic acid (15% w/w) in an aqueous gel base containing benzoic acid (as a preservative), disodium EDTA, lecithin, medium-chain triglycerides, polyacrylic acid, polysorbate 80, propylene glycol, purified water, and sodium hydroxide to adjust pH.

12 CLINICAL PHARMACOLOGY

12.1 Mechanism of Action

The mechanism(s) by which azelaic acid interferes with the pathogenic events in rosacea are unknown.

12.2 Pharmacodynamics

The pharmacodynamics of azelaic acid in association with the treatment of rosacea are unknown.

12.3 Pharmacokinetics

The percutaneous absorption of azelaic acid after topical application of azelaic acid gel could not be reliably determined. Mean plasma azelaic acid concentrations in rosacea subjects treated with azelaic acid gel twice daily for at least 8 weeks are in the range of 42 to 63.1 ng/mL. These values are within the maximum concentration range of 24.0 to 90.5 ng/mL observed in rosacea subjects treated with vehicle only. This indicates that azelaic acid gel does not increase plasma azelaic acid concentration beyond the range derived from nutrition and endogenous metabolism.

In vitro and human data suggest negligible cutaneous metabolism of ^3H-azelaic acid after topical application of 20% azelaic acid cream. Azelaic acid is mainly excreted unchanged in the urine, but undergoes some ß-oxidation to shorter chain dicarboxylic acids.

13 NONCLINICAL TOXICOLOGY

13.1 Carcinogenesis, Mutagenesis, Impairment of Fertility

In a 2-year dermal mouse carcinogenicity study, azelaic acid pre-foam emulsion was administered twice daily to CD-1 mice at topical doses of 5%, 15%, and 30% (500, 1500, and 3000 mg/kg/day azelaic acid). No drug-related tumors were noted at concentrations up to 30% azelaic acid (396 times the MRHD based on AUC comparison).

Azelaic acid was not mutagenic or clastogenic in a battery of in vitro [Ames assay, HGPRT in V79 cells (Chinese hamster lung cells), and chromosomal aberration assay in human lymphocytes] and in vivo (dominant lethal assay in mice and mouse micronucleus assay) genotoxicity tests.

Oral administration of azelaic acid at dose levels up to 2500 mg/kg/day (162 times the MRHD based on BSA comparison) did not affect fertility or reproductive performance in male or female rats.

14 CLINICAL STUDIES

Azelaic acid gel was evaluated for the treatment of mild to moderate papulopustular rosacea in two multicenter, randomized, double-blind, vehicle-controlled, 12-week clinical trials having identical protocols and involving a total of 664 (active: 333; vehicle: 331) subjects aged 21 to 86 years (mean age = 49). Overall, 92.5% of subjects were Caucasian and 73% of subjects were female. Enrolled subjects had mild to moderate rosacea with a mean lesion count of 18 (range 8 to 60) inflammatory papules and pustules. The following subjects were excluded: a) those without papules and pustules; b) those with nodules, rhinophyma, or ocular involvement and c) those with a history of hypersensitivity to propylene glycol or to any other ingredients of the study drug. Azelaic acid gel or its vehicle were to be applied twice daily for 12 weeks; no other topical or systemic medication affecting the course of rosacea and/or evaluability was to be used during the studies. Subjects were instructed to avoid spicy foods, thermally hot food/drink and alcoholic beverages during the study. Subjects were also instructed to use only very mild soaps or soapless cleansing lotion for facial cleansing.

The primary efficacy endpoints included both 1) change from baseline in inflammatory lesion counts as well as 2) success defined as a score of "clear" or "minimal" with at least a 2-step reduction from baseline on the Investigator's Global Assessment (IGA), defined as follows below:

CLEAR:
  No papules and/or pustules; no or residual erythema; no or mild to moderate telangiectasia
MINIMAL:
  Rare papules and/or pustules; residual to mild erythema; mild to moderate telangiectasia
MILD:
  Few papules and/or pustules; mild erythema; mild to moderate telangiectasia
MILD TO MODERATE:
  Distinct number of papules and/or pustules; mild to moderate erythema; mild to moderate telangiectasia
MODERATE:
  Pronounced number of papules and/or pustules; moderate erythema; mild to moderate telangiectasia
MODERATE TO SEVERE:
  Many papules and/or pustules, occasionally with large inflamed lesions; moderate erythema; moderate degree of telangiectasia
SEVERE:
  Numerous papules and/or pustules, occasionally with confluent areas of inflamed lesions; moderate or severe erythema; moderate or severe telangiectasia

Primary efficacy assessment was based on the "intent-to-treat" (ITT) population with the "last observation carried forward" (LOCF).

Both trials demonstrated a statistically significant difference in favor of azelaic acid gel over its vehicle in both reducing the number of inflammatory papules and pustules associated with rosacea (Table 2) as well as demonstrating success on the IGA in the ITT-LOCF population at the end of treatment.

Table 2: Inflammatory Papules and Pustules (ITT population) [ITT population with last observation carried forward (LOCF)]
 | Study One Azelaic Acid Gel, 15% N=164 | Study One VEHICLE N=165 | Study Two Azelaic Acid Gel, 15% N=167 | Study Two VEHICLE N=166
Mean Lesion Count Baseline | 17.5 | 17.6 | 17.9 | 18.5
End of Treatment | 6.8 | 10.5 | 9.0 | 12.1
Mean Percent Reduction End of Treatment | 57.9% | 39.9% | 50.0% | 38.2%

Although some reduction of erythema which was present in subjects with papules and pustules of rosacea occurred in clinical trials, efficacy for treatment of erythema in rosacea in the absence of papules and pustules has not been evaluated.

Azelaic acid gel was superior to the vehicle with regard to success based on the IGA of rosacea on a 7-point static score at the end of treatment (ITT population; Table 3).

Table 3: Investigator's Global Assessment at the End of Treatment [ITT population with last observation carried forward (LOCF)]
 | Study One Azelaic Acid Gel, 15% N=164 | Study One VEHICLE N=165 | Study Two Azelaic Acid Gel, 15% N=167 | Study Two VEHICLE N=166
Clear, Minimal or Mild at End of Treatment (% of Subjects) | 61% | 40% | 61% | 48%

16 HOW SUPPLIED/STORAGE AND HANDLING

How Supplied

Azelaic acid gel, 15% is a white to yellowish white opaque gel supplied in a 50 g tube (NDC 0781-7172-50).

Storage and Handling

Store at 25°C (77°F); excursions permitted between 15-30°C (59-86°F) [see USP Controlled Room Temperature].

17 PATIENT COUNSELING INFORMATION

Inform patients using azelaic acid gel of the following:

Administration Instructions

- For topical use only.
- Before applying azelaic acid gel, cleanse affected area(s) with a very mild soap or a soapless cleansing lotion and pat dry with a soft towel.
- Wash hands immediately following application of azelaic acid gel.
- Cosmetics may be applied after the application of azelaic acid gel has dried.
- Avoid the use of occlusive dressings or wrappings.
- Avoid use of alcoholic cleansers, tinctures and astringents, abrasives and peeling agents [see Dosage and Administration (2)].

Hypersensitivity

- If allergic reactions occur, discontinue use and consult their healthcare provider [see Warnings and Precautions (5.1)].

Skin Irritation

- Skin irritation (e.g., pruritus, burning, or stinging) may occur during use of azelaic acid gel, usually during the first few weeks of treatment. If irritation is excessive or persists, or allergic reactions occur, discontinue use and consult your physician [see Warnings and Precautions (5.2)].

Hypopigmentation

- Advise patients to report abnormal changes in skin color to their healthcare provider [see Warnings and Precautions (5.2)].

Eye and Mucous Membranes Irritation

- Avoid contact with the eyes, mouth and other mucous membranes. If azelaic acid gel comes in contact with the eyes, wash the eyes with large amounts of water and consult their healthcare provider if eye irritation persists [see Warnings and Precautions (5.3)].

Exacerbation of Asthma

- Advise patients to report any worsening of asthma to their healthcare provider [see Warnings and Precautions (5.4)].

© 2021, LEO Pharma Inc. All rights reserved.

Manufactured for
LEO Pharma A/S
Industriparken 55
Ballerup, 2750, Denmark

Distributed by
Sandoz Inc.
Princeton, NJ 08540

PACKAGE/LABEL PRINCIPAL DISPLAY PANEL

NDC 0781-7172-50

Azelaic Acid Gel

15%

Rx Only

50 grams

SANDOZ

A Novartis Division